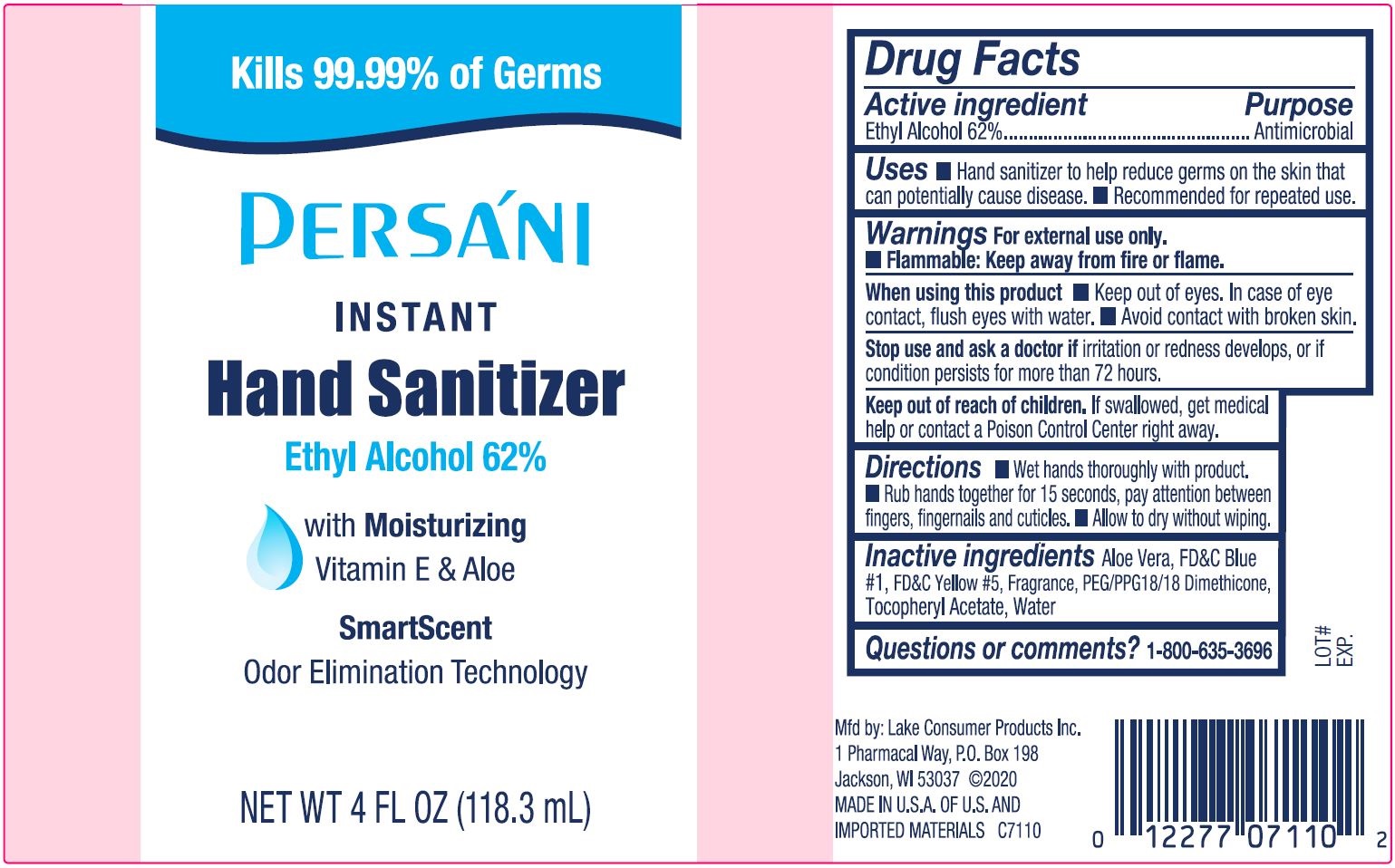 DRUG LABEL: Persani Instant Hand Sanitizer
NDC: 68093-7110 | Form: LIQUID
Manufacturer: Wisconsin Pharmacal Company
Category: otc | Type: HUMAN OTC DRUG LABEL
Date: 20220113

ACTIVE INGREDIENTS: ALCOHOL 62 mL/100 mL
INACTIVE INGREDIENTS: ALPHA-TOCOPHEROL ACETATE; ALOE VERA LEAF; WATER; FD&C BLUE NO. 1; FD&C YELLOW NO. 5; PEG/PPG-18/18 DIMETHICONE

Persani Instant Hand Sanitizer

Purpose

Hand sanitizer to help reduce germs on the on the skin that can potentially cause disease

Drug Facts

Active Ingredient

Active ingredient | Purpose
Ethyl Alcohol 62% | Antimicrobial

Use

• Hand sanitizer to help reduce germs on the on the skin that can potentially cause disease. • Recomended for repeated use.

Warnings

- For external use only.
- Flammable: Keep away from heat or flame

When using this product • Keep out of eyes. In case of eye contact, flush eyes with water. Avoid contact with broken skin.

Stop use and ask a doctor if irritation or redness develops, or if condition persist for more than 72 hours.

Keep out of reach of children. If swallowed, get medical help or contact a Poison Control Center right away.

Directions

- Wet hands throughly with product.
- Rub hands together for 15 seconds, pay attention between fingers, fingernails and cuticles.
- Allow to dry without wiping.

Inactive ingredients

Aloe Vera, FD&C Blue#1, FD&C Yellow #5, Fragrance, PEG/PPG18/18 Dimethicone, Tocopheryl Acetate, Water

Questions or comments?

1-800-635-3696

Package Label - Principal Display Panel

Kills 99.99% of Germs

PERSANI

Instant

Hand Sanitizer

Ethyl Alcohol 62%

with Moisturizing

Vitamin E & Aloe

SmartScent

Odor Elimination Technology

NET WT 4 FL OZ (118.3 mL)